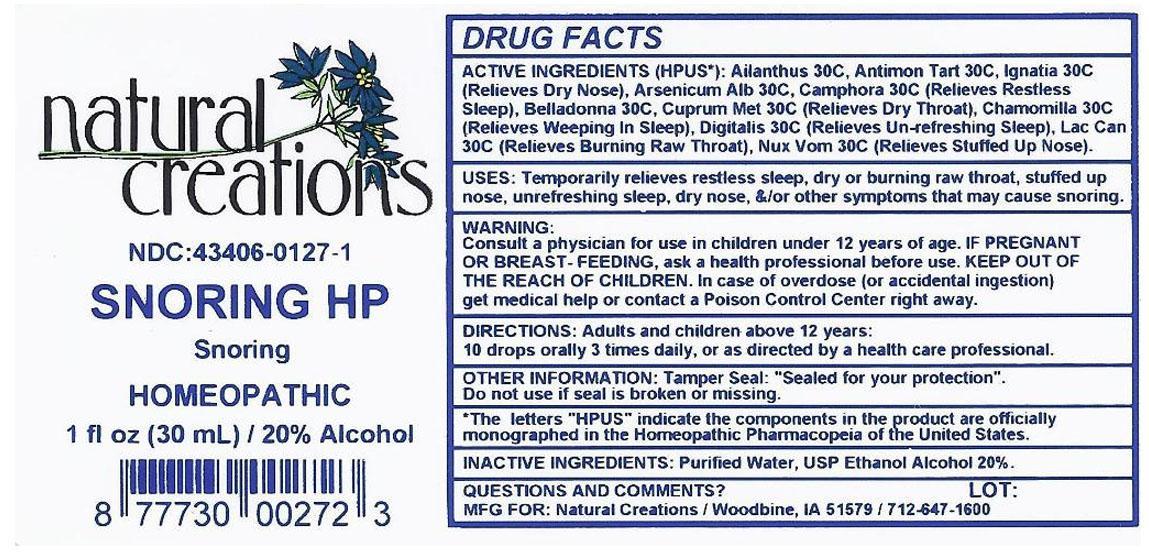 DRUG LABEL: SNORING HP
NDC: 43406-0127 | Form: LIQUID
Manufacturer: Natural Creations, Inc.
Category: homeopathic | Type: HUMAN OTC DRUG LABEL
Date: 20121120

ACTIVE INGREDIENTS: AILANTHUS ALTISSIMA FLOWERING TWIG 30 [hp_C]/1 mL; ANTIMONY POTASSIUM TARTRATE 30 [hp_C]/1 mL; ARSENIC TRIOXIDE 30 [hp_C]/1 mL; ATROPA BELLADONNA 30 [hp_C]/1 mL; CAMPHOR (NATURAL) 30 [hp_C]/1 mL; CHAMOMILE 30 [hp_C]/1 mL; COPPER 30 [hp_C]/1 mL; DIGITALIS 30 [hp_C]/1 mL; STRYCHNOS IGNATII SEED 30 [hp_C]/1 mL; CANIS LUPUS FAMILIARIS MILK 30 [hp_C]/1 mL; STRYCHNOS NUX-VOMICA SEED 30 [hp_C]/1 mL
INACTIVE INGREDIENTS: WATER; ALCOHOL

SNORING HP

ACTIVE INGREDIENT

ACTIVE INGREDIENTS (HPUS*): Ailanthus Glandulosus 30C, Antimonium Tartaricum 30C, Arsenicum Album 30C, Belladonna 30C, Camphora 30C, Chamomilla 30C, Curprum metallicum 30C, Digitalis Purpurea 30C, Ignatia Amara 30C, Lac Caninum 30C, Nux Vomica 30C

INDICATIONS AND USAGE

USES: Temporarily relieves restless sleep, dry or burning raw throat, stuffed up nose, unrefreshing sleep, dry nose, &/or other symptoms that may cause snoring.

WARNING:

Consult a physician for use in children under 12 years of age. IF PREGNANT OR BREAST-FEEDING, ask a health care professional before use. KEEP OUT OF THE REACH OF CHILDREN. In case of overdose (or accidental ingestion) get medical help or contact a Poison Control Center right away.

DOSAGE AND ADMINISTRATION

DIRECTIONS: Adults and children above 12 years: 10 drops orally 3 times daily, or as directed by a health care professional.

OTHER INFORMATION: Tamper Seal: "Sealed for your protection."

Do not use if seal is broken or missing.

REFERENCES

*The letters "HPUS" indicate the components in the product are officially monographed in the Homeopathic Pharmacopeia of the United States.

INACTIVE INGREDIENTS: Purified Water, USP Ethanol Alcohol 20%

QUESTIONS AND COMMENTS?

MFG FOR: Natural Creations / Woodbine, IA / 51579 712.647.1600

LOT:

PURPOSE

USES: Temporarily relieves restless sleep, dry or burning raw throat, stuffed up nose, unrefreshing sleep, dry nose, &/or other symptoms that may cause snoring.

KEEP OUT OF REACH OF CHILDREN

KEEP OUT OF THE REACH OF CHILDREN. In case of overdose (or accidental ingestion) get medical help or contact a Poison Control Center.

PACKAGE LABEL

NDC: 43406-0127-1

SNORING HP

Snoring

HOMEOPATHIC

1 fl oz (30 mL) / 20% Alcohol

UPC: 877730002723